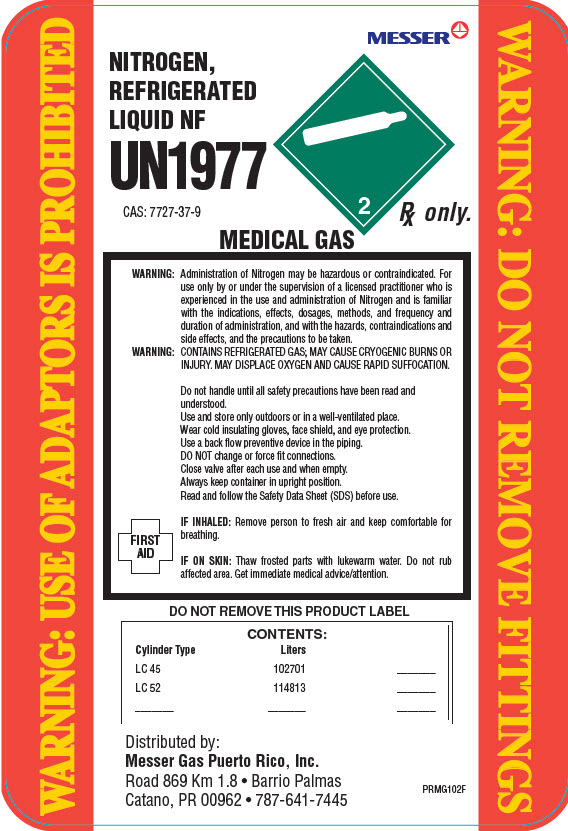 DRUG LABEL: Nitrogen
NDC: 52374-102 | Form: GAS
Manufacturer: Messer Gas Puerto Rico, Inc
Category: prescription | Type: HUMAN PRESCRIPTION DRUG LABEL
Date: 20251118

ACTIVE INGREDIENTS: NITROGEN 99 L/100 L

Messer PR - NITROGEN, REFRIGERATED LIQUID -102

WARNINGS AND PRECAUTIONS SECTION

WARNING:Administration of Nitrogen may be hazardous or contraindicated. For use only by or under the supervision of a licensed practitioner who is experienced in the use and administration of Nitrogen and is familiar with the indications, effects, dosages, methods, and frequency and duration of administration, and with the hazards, contraindications and side effects, and the precautions to be taken.
WARNING: CONTAINS REFRIGERATED GAS; MAY CAUSE CRYOGENIC BURNS OR INJURY. MAY DISPLACE OXYGEN AND CAUSE RAPID SUFFOCATION.

PACKAGE LABEL

Messer

NITROGEN, REFRIGERATED LIQUID NF

UN1977

CAS: 7727-37-9

2

Rx only.

MEDICAL GAS

WARNING: USE OF ADAPTORS IS PROHIBITED
WARNING: DO NOT REMOVE FITTINGS

Rx only

Do not handle until all safety precautions have been read and understood. Use and store only outdoors or in a well-ventilated place. Wear cold insulating gloves, face shield, and eye proteciton. Use a back flow preventive device in the piping. DO NOT change or force fit connections. Close valve after each use and when empty. Always keep container in upright position. Read and follow the Safety Data Sheet (SDS) before use.

FIRST AID

IN INHALED: Remove person to fresh air and keep comfortable for breathing.
IF ON SKIN:Thaw frosted parts with lukewarm water. Do not rub affected area. Get immediate medical advice/attention.

DO NOT REMOVE THIS PRODUCT LABEL

CONTENTS:
Cylinder Type | Liters
LC 45 | 102701 | _______
LC 52 | 114813 | _______
_______ | _______ | _______

Distributed by:
Messer Gas Puerto Rico, Inc.
Road 869 km 1.8
Barrio Palmas
Catano, PR 00962
787-641-7445

PRMG102F